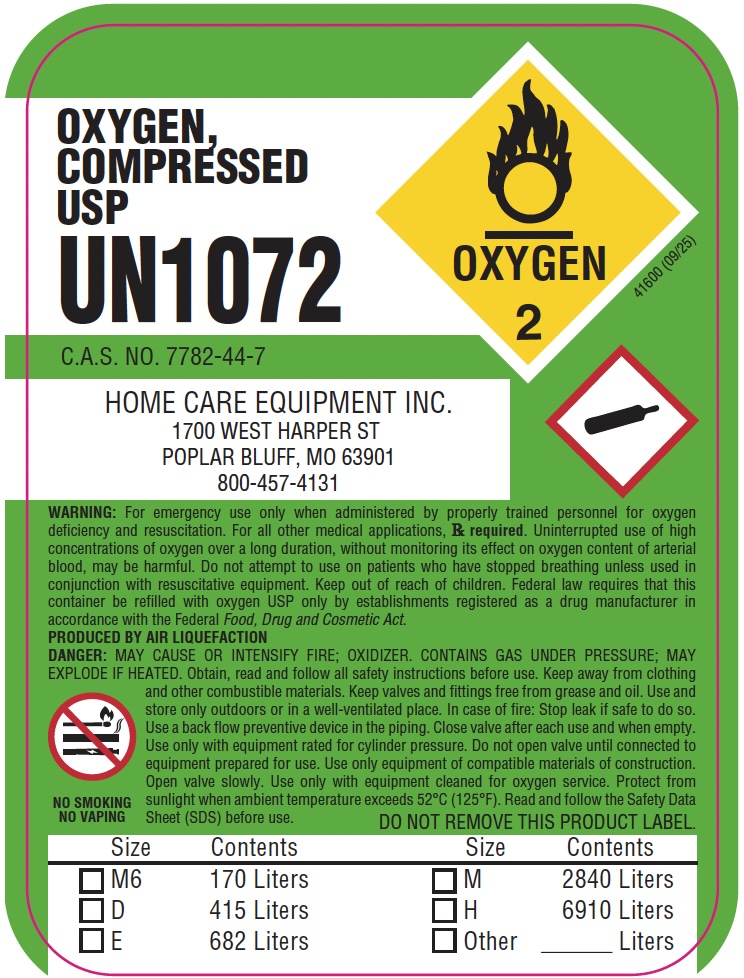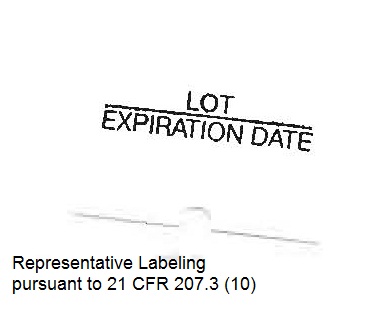 DRUG LABEL: Oxygen
NDC: 57959-123 | Form: GAS
Manufacturer: Home Care Equipment, Inc.
Category: prescription | Type: HUMAN PRESCRIPTION DRUG LABEL
Date: 20251222

ACTIVE INGREDIENTS: OXYGEN 99 L/100 L

Oxygen, USP

Principal for Oxygen Product

OXYGEN,

COMPRESSED

USP

UN1072

C.A.S. NO. 7782-44-7

OXYGEN

2

HOME CARE EQUIPMENT INC.

1700 WEST HARPER ST

POPLAR BLUFF, MO 63901

800-457-4131

WARNING: For emergency use only when administered by properly trained personnel for oxygen deficiency and resuscitation. For all other medical applications, Rx required. Uninterrupted use of high concentrations of oxygen over a long duration, without monitoring its effect on oxygen content of arterial blood, may be harmful. Do not attempt to use on patients who have stopped breathing unless used in conjunction with resuscitative equipment. Keep out of reach of children. Federal law requires that this container be refilled with oxygen USP only by establishments registered as a drug manufacturer in accordance with the Federal Food, Drug and Cosmetic Act.

PRODUCED BY AIR LIQUEFACTION

DANGER: MAY CAUSE OR INTENSIFY FIRE; OXIDIZER. CONTAINS GAS UNDER PRESSURE; MAY EXPLODE IF HEATED. Obtain, read and follow all safety instructions before use. Keep away from clothing and other combustible materials. Keep valves and fittings free from grease and oil. Use and store only outdoors or in a well-ventilated place. In case of fire: Stop leak if safe to do so. Use a back flow preventive device in the piping. Close valve after each use and when empty. Use only with equipment rated for cylinder pressure. Do not open valve until connected to equipment prepared for use. Use only equipment of compatible materials of construction. Open valve slowly. Use only with equipment cleaned for oxygen service. Protect from sunlight when ambient temperature exceeds 52°C (125°F). Read and follow the Safety Data Sheet (SDS) before use.

NO SMOKING

NO VAPING

Size / Contents

☐ M6 — 170 Liters

☐ D — 415 Liters

☐ E — 682 Liters

☐ M — 2840 Liters

☐ H — 6910 Liters

☐ Other ______ Liters

DO NOT REMOVE THIS PRODUCT LABEL